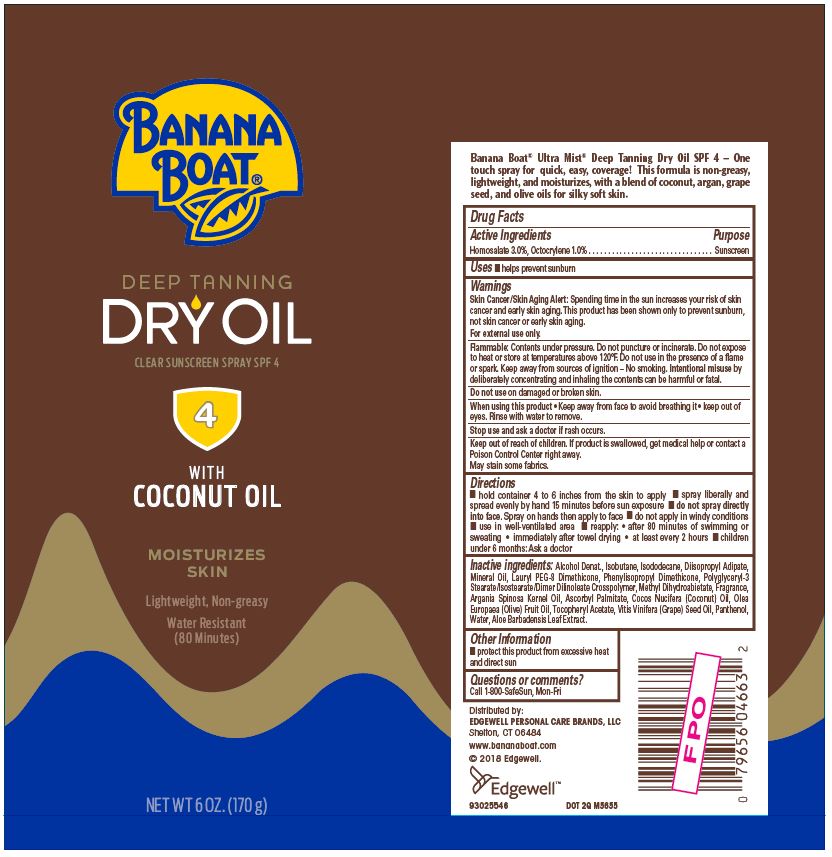 DRUG LABEL: BANANA BOAT
NDC: 63354-323 | Form: SPRAY
Manufacturer: Edgewell Personal Care Brands, LLC
Category: otc | Type: HUMAN OTC DRUG LABEL
Date: 20231125

ACTIVE INGREDIENTS: HOMOSALATE 3 g/100 g; OCTOCRYLENE 1 g/100 g
INACTIVE INGREDIENTS: ALCOHOL; ISOBUTANE; ISODODECANE; DIISOPROPYL ADIPATE; MINERAL OIL; METHYL DIHYDROABIETATE; ARGAN OIL; ASCORBYL PALMITATE; PANTHENOL; ALOE VERA LEAF; WATER

Active Ingredients

Homosalate 3.0%, Octocrylene 1.0%

Purpose

Sunscreen

Uses

helps prevent sunburn

Warnings

Skin Cancer/Skin Aging Alert: Spending time in the sun increases your risk of skin cancer and early sin aging. This product has been shown only to prevent sunburn, not skin cancer or early skin aging. For external use only.

For external use only.

May stain some fabrics.

Flammable

Do not puncture or incinerate. Contents under pressure. Do not expose to heat or store at temperatures above 120F. Do not use in the presence of a flame or spark. Keep away from sources of ignition-No smoking. Intentional misuse by deliberately concentrating and inhaling the contents can be harmful or fatal.

Do not use

on damaged or broken skin.

When using this product

• Keep away from face to avoid breathing it • keep out of eyes. Rinse with water to remove.

Stop use and ask a doctor

if rash occurs.

Keep out of reach of children.

If product is swallowed, get medical help or contact a Poison Control Center right away.

Directions

• hold container 4 to 6 inches from the skin to apply • spray liberally and spread evenly by hand 15 minutes before sun exposure • do not spray directly into face. Spray on hands then apply to face • do not apply in windy conditions • use in well-ventilated area • reapply: • after 80 minutes of swimming or sweating • immediately after towel drying, • at least every 2 hours • children under 6 months: Ask a doctor.

Inactive ingredients

Alcohol Denat., Isobutane, Isododecane, Diisopropyl Adipate, Mineral Oil, Lauryl PEG-8 Dimethicone, Phenylisopropyl Dimethicone, Polyglyceryl-3 Stearate/Isostearate/Dimer Dilinoleate Crosspolymer, Methyl Dihydroabietate, Fragrance, Argania Spinosa Kernel Oil, Ascorbyl Palmitate, Cocos Nucifera (Coconut) Oil, Olea Europaea (Olive) Fruit Oil, Tocopheryl Acetate, Vitis Vinifera (Grape) Seed Oil, Panthenol, Water, Aloe Barbadensis Leaf Extract.

Other Information

• protect this product from excessive heat and direct sun

Principal Display Panel

BANANA
BOAT®
DEEP TANNING
DRY OIL
CLEAR SUNSCREEN SPRAY SPF 4
4
WITH
COCONUT OIL
MOISTURIZES
SKIN
Lightweight, Non-greasy
Water Resistant
(80 Minutes)
NET WT 6 OZ. (170 g)